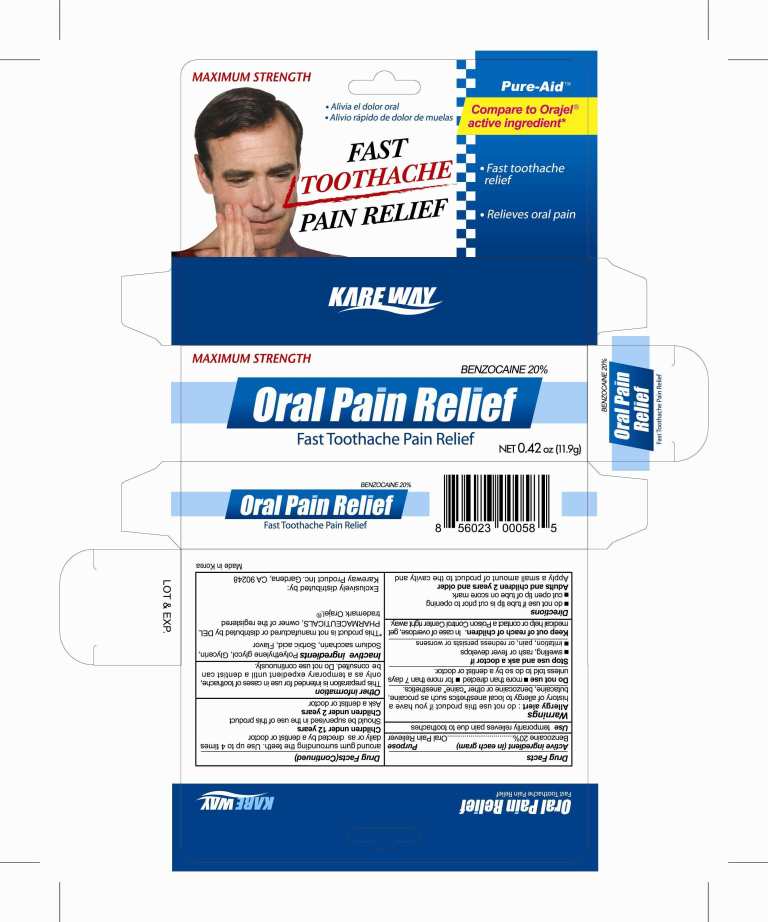 DRUG LABEL: Oral Pain Relief
NDC: 67510-0058 | Form: GEL
Manufacturer: Kareway Product, Inc.
Category: otc | Type: HUMAN OTC DRUG LABEL
Date: 20171227

ACTIVE INGREDIENTS: BENZOCAINE 200 mg/1 g
INACTIVE INGREDIENTS: POLYETHYLENE GLYCOL; SACCHARIN SODIUM; SORBIC ACID; GLYCERIN

Drug Facts

Warnings

Allergy alert: do not use this product if you have a history of allergy to local anesthetics such as procaine, butacaine, benzocaine or other "caine" anesthetics

Do not use

more than directed for more than 7 days unless told to do so by a dentist or doctor

Stop use and ask a doctor if

swelling, rash or fever develops; irritation, pain or redness persists or worsens; symptoms do not improve in 7 days

Keep out of reach of children:

in case of overdose, get medical help or contact a Poison Control Center right away

Directions

Directions do not use if tube tip is cut prior to opening; cut open tip of tube on score mark

Adults and children 2 years of age and over Apply a small amount of product to the cavity and around gum surrounding the teeth.
Use up to 4 times daily or as directed by a dentist or doctor

Children under 12 years of age Should be supervised in the use of this product
Children under 2 years of age Ask a dentist or doctor
Other information

This preparation is intended for use in case of toothache, only as a temporary expedient until a dentist can be consulted;
do not use continuously

Inactive ingredients

Inactive ingredients polyethylene glycol, glycerin, sodium saccharin, sorbic acid, flavor

Active ingredient (in each gram)

Benzocaine 20%

Purpose

Oral Pain Reliever

Uses

temporarily relieves pain due to toothaches

PACKAGE LABEL

Orajel gel

Instant Pain Relief

for TOOTHACHE

MAXIMUM STRENGTH

NE WT 0.42 OZ (11.9 g) ORAL PAIN RELIEVER BENZOCAINE 20%